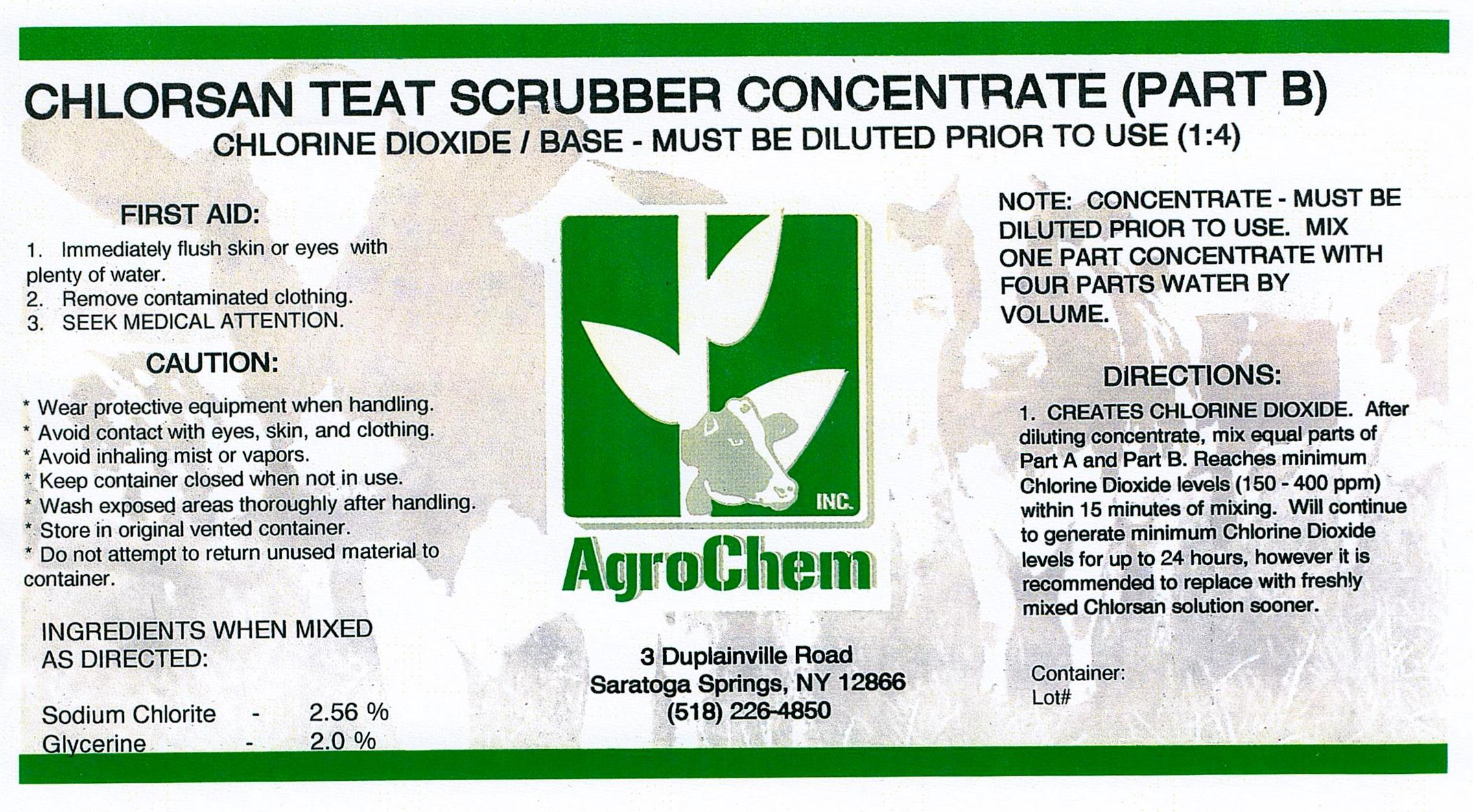 DRUG LABEL: Chlorsan Concentrate Teat Scrubber Part B
NDC: 17307-3654 | Form: SOLUTION
Manufacturer: AgroChem Inc
Category: animal | Type: OTC ANIMAL DRUG LABEL
Date: 20131031

ACTIVE INGREDIENTS: SODIUM CHLORITE 0.0256 kg/1 kg
INACTIVE INGREDIENTS: GLYCERIN 0.02 kg/1 kg

Chlorsan Teat Scrubber Concentrate Part B

DESCRIPTION

CHLORINE DIOXIDE / BASE - MUST BE DILUTED PRIOR TO USE (1:4)

WARNINGS AND PRECAUTIONS

FIRST AID:

1. Immediately flush skin or eyes with

plenty of water.

2. Remove contaminated clothing.

3. SEEK MEDICAL ATTENTION.

CAUTION:

* Wear protective equipment when handling.

* Avoid contact with eyes, skin, and clothing.

* Avoid inhaling mist or vapors.

* Keep container closed when not in use.

* Wash exposed areas thoroughly after handling.

* Store in original vented container.

* Do not attempt to return unused material to

container.

ACTIVE INGREDIENT

INGREDIENTS WHEN MIXED AS DIRECTED:

Sodium Chlorite - 2.56 %

Glycerine - 2.0 %

INSTRUCTIONS FOR USE

NOTE: CONCENTRATE - MUST BE

DILUTED PRIOR TO USE. MIX

ONE PART CONCENTRATE WITH

FOUR PARTS WATER BY

VOLUME.

DIRECTIONS:

1. CREATES CHLORINE DIOXIDE. After

diluting concentrate, mix equal parts of

Part A and Part B. Reaches minimum

Chlorine Dioxide levels (150 - 400 ppm)

within 15 minutes of mixing. Will

continue to generate minimum Chlorine

Dioxide levels for up to 24 hours, however

it is recommended to replace with

freshly mixed Chlorsan solution sooner.